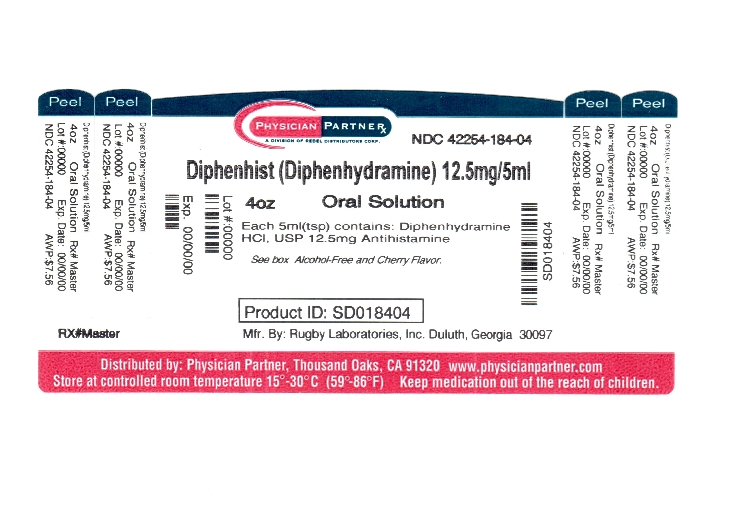 DRUG LABEL: Diphenhist
NDC: 42254-184 | Form: LIQUID
Manufacturer: Rebel Distributors Corp
Category: otc | Type: HUMAN OTC DRUG LABEL
Date: 20120320

ACTIVE INGREDIENTS: Diphenhydramine Hydrochloride 12.5 mg/5 mL
INACTIVE INGREDIENTS: Citric Acid Monohydrate; D&C RED NO. 33; FD&C RED NO. 40; Glycerin; Polysorbate 20; Water; Sodium Benzoate; Sodium Citrate; SACCHARIN SODIUM DIHYDRATE; Sorbitol

Diphenhist

Drug Facts

Active ingredient (in each 5mL teaspoonful)

Diphenhydramine HCl USP 12.5 mg

Purpose

Antihistamine

Uses

temporarily relieves these symptoms of hay fever or other upper respiratory allergies

- runny nose
- sneezing
- itchy, water eyes
- itchy nose or throat

Warnings

Do not use with any other product containing diphenhydramine, even one used on skin

Ask a doctor before use if you have

- glaucoma
- trouble urinating due to an enlarged prostate gland
- a breathing problem such as emphysema or chronic bronchitis

Ask a doctor or pharmacist before use if you are taking sedatives or tranquilizers

When using this product

- you may get very drowsy
- avoid alcoholic drinks
- alcohol, sedatives, and tranquilizers may increase drowsiness
- be careful when driving a motor vehicle or operating machinery
- excitability may occur, especially in children

PREGNANCY OR BREAST FEEDING

If pregnant or breast-feeding, ask a health professional before use.

Keep out of reach of children. In case of overdose, get medical help or contact a Poison Control Center right away.

Directions

- take every 4 – 6 hours
- do not take more than 6 doses in 24 hours

adults and children 12 years and over | 2 - 4 teaspoonfuls
children 6 to under 12 years | 1 - 2 teaspoonfuls
children under 6 | do not use

Other information

- each teaspoonful (5 mL) contains:
  sodium 5 mg
- store between 20°-25° C (68°-77°F)
- protect from light. Store in outer carton until contents used

Inactive ingredients

artificial cherry flavor, citric acid, D&C red #33, FD&C red #40, glycerin, polysorbate 20, purified water, saccharin sodium, sodium benzoate, sodium citrate, sorbitol solution

Questions or comments?

call 1-800-645-2158, 9 am - 5pm ET, Monday - Friday

PRINCIPAL DISPLAY PANEL

COMPARE TO
ACTIVE INGREDIENT IN
BENADRYL®
ALLERGY LIQUID*

CHILDREN'S ALCOHOL-FREE
ALLERGY MEDICATION

Diphenhist®

ORAL SOLUTION

Diphenydramine HCI, USP

Antihistamine

For Temporary Relief of

Symptoms of Upper

Respiratory Allergies

and Hay Fever

4 fl oz
(118 mL)